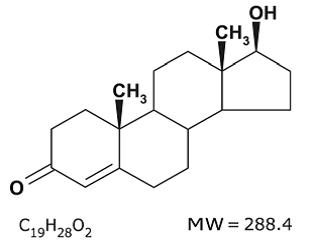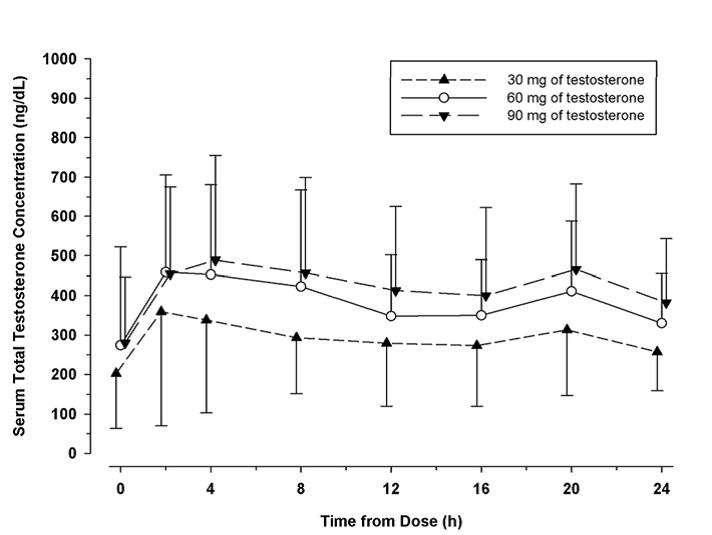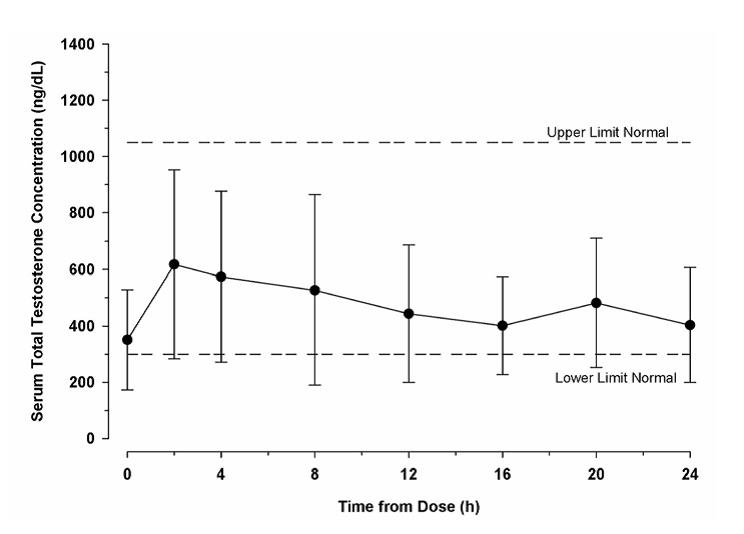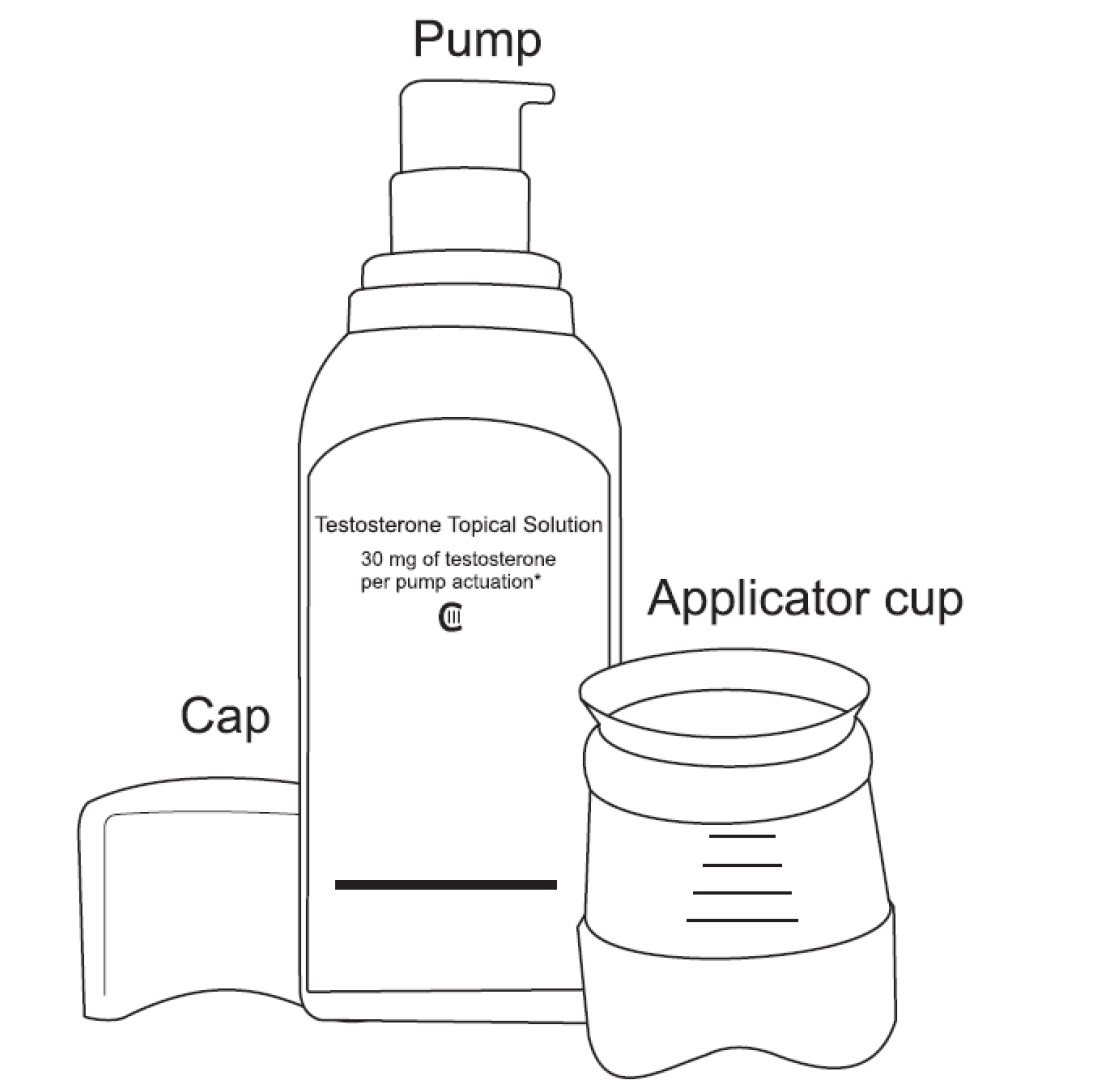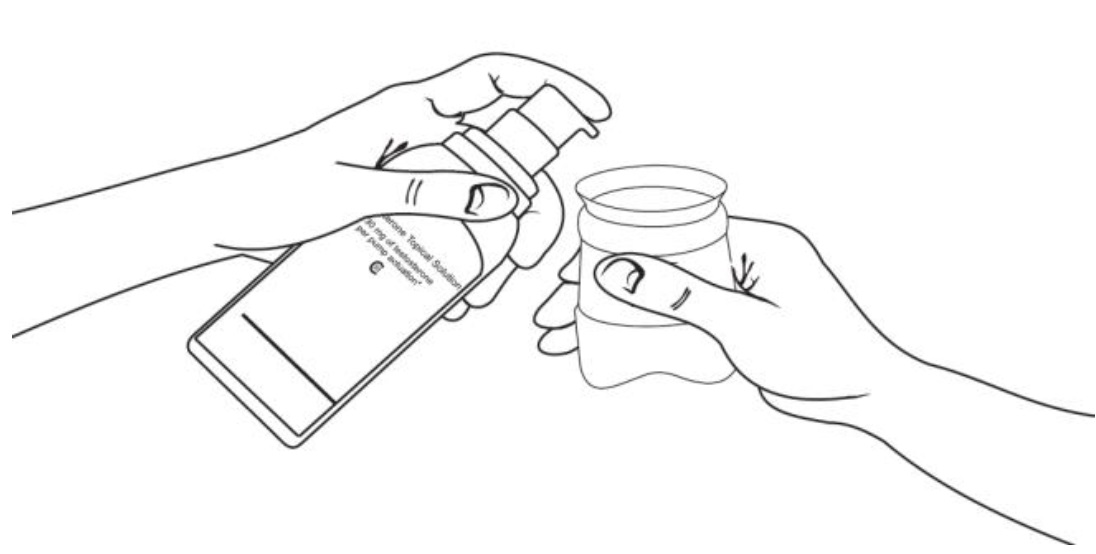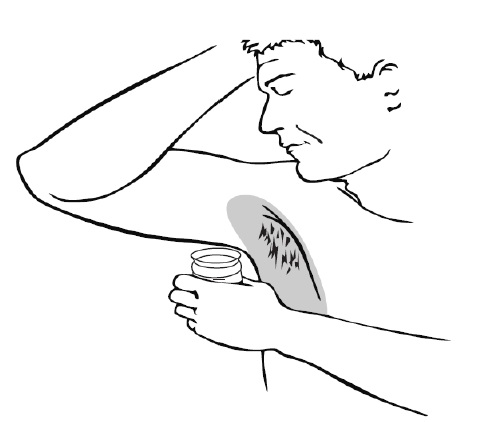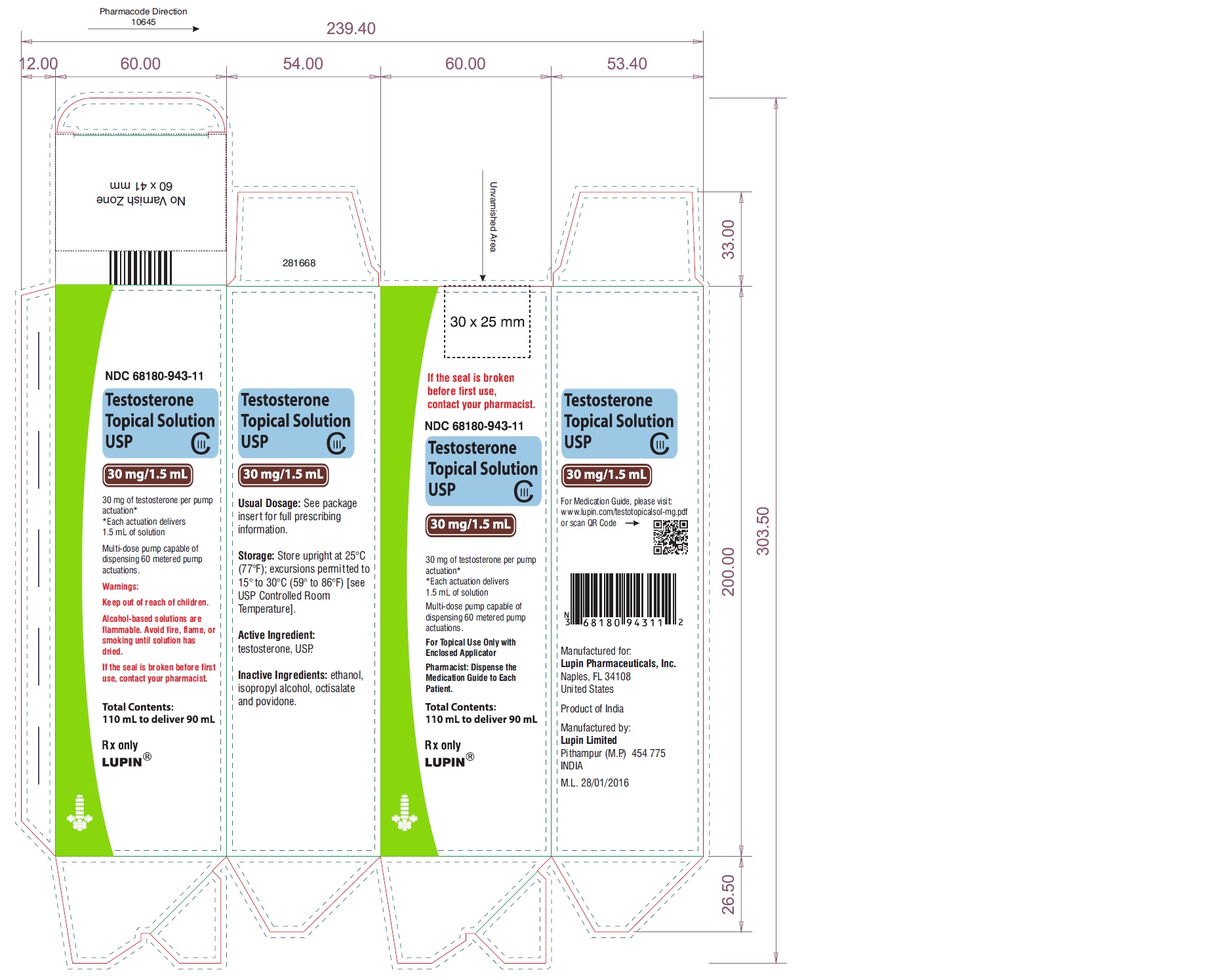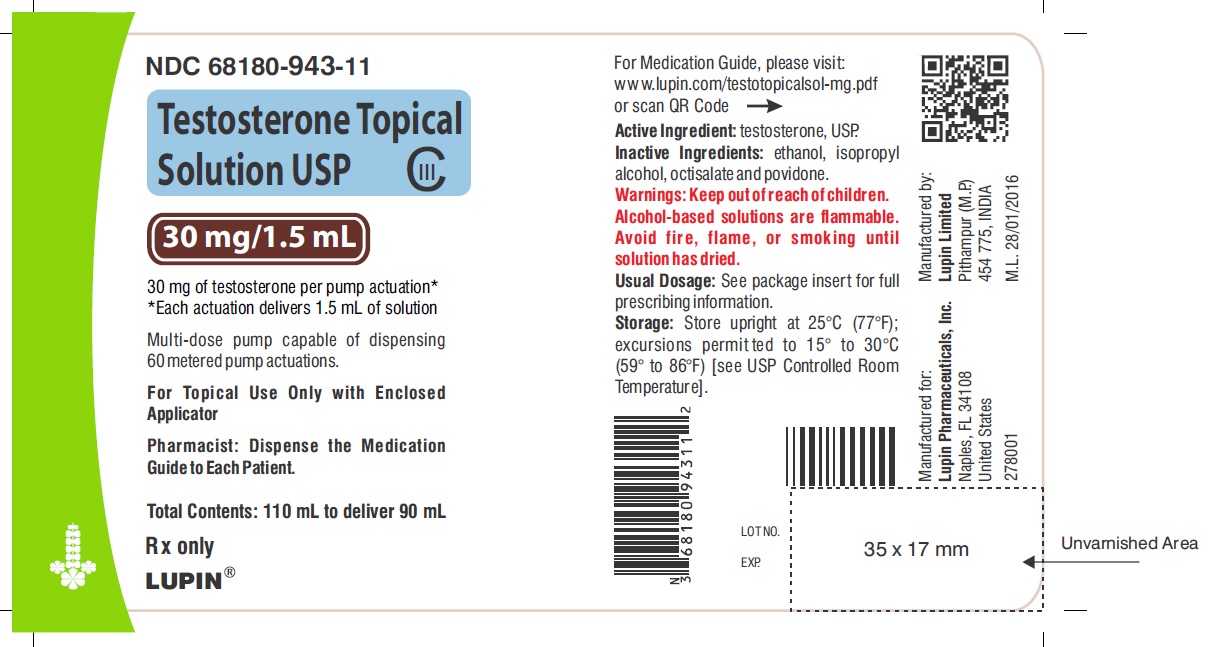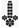 DRUG LABEL: Testosterone
NDC: 68180-943 | Form: SOLUTION
Manufacturer: Lupin Pharmaceuticals, Inc.
Category: prescription | Type: HUMAN PRESCRIPTION DRUG LABEL
Date: 20260113
DEA Schedule: CIII

ACTIVE INGREDIENTS: TESTOSTERONE 30 mg/1.5 mL
INACTIVE INGREDIENTS: ALCOHOL; ISOPROPYL ALCOHOL; OCTISALATE; POVIDONE

HIGHLIGHTS OF PRESCRIBING INFORMATION

These highlights do not include all the information needed to use TESTOSTERONE TOPICAL SOLUTION USP safely and effectively. See full prescribing information for TESTOSTERONE TOPICAL SOLUTION USP.
TESTOSTERONE topical solution USP, for topical use, CIII
Initial U.S. Approval: 1953

WARNING: SECONDARY EXPOSURE TO TESTOSTERONE

See full prescribing information for complete boxed warning.

- Virilization has been reported in children who were secondarily exposed to topical testosterone products (5.2)
- Children should avoid contact with unwashed or unclothed application sites in men using testosterone topical solution (2.2, 5.2)
- Healthcare providers should advise patients to strictly adhere to recommended instructions for use (2.2,5.2, 17)

RECENT MAJOR CHANGES

Warnings and Precautions (5.6) 03/2025

1 INDICATIONS AND USAGE

Testosterone topical solution USP is indicated for replacement therapy in males for conditions associated with a deficiency or absence of endogenous testosterone:

- Primary hypogonadism (congenital or acquired) (1)
- Hypogonadotropic hypogonadism (congenital or acquired) (1)

Limitations of use:

- Safety and efficacy of testosterone topical solution USP in men with "age-related hypogonadism" have not been established. (1)
- Safety and efficacy of testosterone topical solution USP in males <18 years old have not been established (8.4)

2 DOSAGE AND ADMINISTRATION

Prior to initiating testosterone topical solution USP, confirm the diagnosis of hypogonadism by ensuring that serum testosterone has been measured in the morning on at least two separate days and that these concentrations are below the normal range (2).

- Starting testosterone topical solution USP dose is 60 mg of testosterone (1 pump actuation of 30 mg of testosterone to each axilla), applied once daily, at the same time each morning. (2.1)
- Apply to clean, dry intact skin of the axilla, not to any other parts of the body including the abdomen or genitals (2.2)
- Dose adjustment: The dose of testosterone may be decreased from 60 mg (2 pump actuations) to 30 mg (1 pump actuation) or increased from 60 mg to 90 mg (3 pump actuations) or from 90 mg to 120 mg (4 pump actuations) based on the serum testosterone concentration from a single blood draw 2 to 8 hours after applying testosterone topical solution USP and at least 14 days after starting treatment or following dose adjustment. (2.2)
- Patients should wash hands immediately with soap and water after applying testosterone topical solution USP and cover the application site with clothing after the solution has dried. Wash the application site thoroughly with soap and water prior to any situation where skin-to-skin contact of the application site with another person is anticipated. (2.2)
- The application site and dose of testosterone topical solution USP are not interchangeable with other topical testosterone products. (2.1)

3 DOSAGE FORMS AND STRENGTHS

Testosterone topical solution is available as follows:

- a metered-dose pump that delivers 30 mg of testosterone per pump.

Each metered-dose pump is supplied with an applicator. (3)

4 CONTRAINDICATIONS

- Men with carcinoma of the breast or known or suspected carcinoma of the prostate (4, 5.1)
- Pregnant or breastfeeding women. Testosterone may cause fetal harm (4, 8.1, 8.3)

5 WARNINGS AND PRECAUTIONS

- Monitor patients with benign prostatic hyperplasia (BPH) for worsening of signs and symptoms of BPH (5.1)
- Avoid unintentional exposure of women or children to testosterone topical solution. Secondary exposure to testosterone can produce signs of virilization. Testosterone topical solution should be discontinued until the cause of the virilization is identified (2.2, 5.2)
- Venous thromboembolism (VTE), including deep vein thrombosis (DVT) and pulmonary embolism (PE) have been reported in patients using testosterone products. Evaluate patients with signs or symptoms consistent with DVT or PE. (5.4)
- Some postmarketing studies have shown an increased risk of myocardial infarction and stroke associated with use of testosterone replacement therapy. (5.5)
- Exogenous administration of testosterone may lead to azoospermia (5.9)
- Edema with or without congestive heart failure, may be a complication in patients with preexisting cardiac, renal, or hepatic disease (5.11).
- Sleep apnea may occur in those with risk factors (5.13)
- Monitor serum testosterone, prostate specific antigen (PSA), liver function, lipid concentrations, hematocrit and hemoglobin periodically (5.1, 5.3, 5.10, 5.14)
- Testosterone topical solution is flammable until dry (5.17)

6 ADVERSE REACTIONS

Most common adverse reactions (incidence >4%) are skin application site reactions, increased hematocrit, headache, diarrhea, vomiting, and increased serum PSA (6.1).

To report SUSPECTED ADVERSE REACTIONS, contact Lupin Pharmaceuticals, Inc. at 1-800-399-2561 or FDA at 1-800-FDA-1088 or www.fda.gov/medwatch.

7 DRUG INTERACTIONS

- Androgens may decrease blood glucose and insulin requirement in diabetic patients (7.1).
- Changes in anticoagulant activity may be seen with androgens. More frequent monitoring of International Normalized Ratio (INR) and prothrombin time is recommended (7.2).
- Use of testosterone with Adrenocorticotropic Hormone (ACTH) or corticosteroids may result in increased fluid retention. Use with caution, particularly in patients with cardiac, renal, or hepatic disease (7.3).

8 USE IN SPECIFIC POPULATIONS

- There are insufficient long-term safety data in geriatric patients using testosterone topical solution to assess the potential risks of cardiovascular disease and prostate cancer (8.5).

FULL PRESCRIBING INFORMATION

WARNING: SECONDARY EXPOSURE TO TESTOSTERONE

- Virilization has been reported in children who were secondarily exposed to topical testosterone products [see WARNINGS AND PRECAUTIONS (5.2)] .
- Children should avoid contact with unwashed or unclothed application sites in men using testosterone topical solution [see DOSAGE AND ADMINISTRATION (2.2) and WARNINGS AND PRECAUTIONS (5.2)] .
- Healthcare providers should advise patients to strictly adhere to recommended instructions for use [see DOSAGE AND ADMINISTRATION (2.2), WARNINGS AND PRECAUTIONS (5.2) and PATIENT COUNSELING INFORMATION (17)] .

RECENT MAJOR CHANGES

Warnings and Precautions (5.6) 03/2025

1 INDICATIONS AND USAGE

Testosterone topical solution USP is indicated for replacement therapy in males for conditions associated with a deficiency or absence of endogenous testosterone:

- Primary hypogonadism (congenital or acquired): testicular failure due to conditions such as cryptorchidism, bilateral torsion, orchitis, vanishing testis syndrome, orchiectomy, Klinefelter's syndrome, chemotherapy, or toxic damage from alcohol or heavy metals. These men usually have low serum testosterone concentrations and gonadotropins (FSH, LH) above the normal range.
- Hypogonadotropic hypogonadism (congenital or acquired): gonadotropin or luteinizing hormone-releasing hormone (LHRH) deficiency or pituitary-hypothalamic injury from tumors, trauma, or radiation. These men have low testosterone serum concentrations but have gonadotropins in the normal or low range.

Limitations of use:

- Safety and efficacy of testosterone topical solution USP in men with "age-related hypogonadism" (also referred to as "late-onset hypogonadism") have not been established.
- Safety and efficacy of testosterone topical solution USP in males <18 years old have not been established [see USE IN SPECIFIC POPULATIONS (8.4)] .

2 DOSAGE AND ADMINISTRATION

Prior to initiating testosterone topical solution USP, confirm the diagnosis of hypogonadism by ensuring that serum testosterone concentrations have been measured in the morning on at least two separate days and that these serum testosterone concentrations are below the normal range.

2.1 Dosing and Dose Adjustment

The recommended starting dose of testosterone topical solution USP is 60 mg of testosterone (2 pump actuations) applied once daily.

To ensure proper dosing, serum testosterone concentrations should be measured after initiation of therapy to ensure that the desired concentrations (300 ng/dL to 1050 ng/dL) are achieved. The testosterone topical solution USP dose can be adjusted based on the serum testosterone concentration from a single blood draw 2 to 8 hours after applying testosterone topical solution USP and at least 14 days after starting treatment or following dose adjustment.

If the measured serum testosterone concentration is below 300 ng/dL, the daily testosterone dose may be increased from 60 mg (2 pump actuations) to 90 mg (3 pump actuations) or from 90 mg to 120 mg (4 pump actuations). If the serum testosterone concentration exceeds 1050 ng/dL, the daily testosterone dose should be decreased from 60 mg (2 pump actuations) to 30 mg (1 pump actuation) as instructed by a physician. If the serum testosterone concentration consistently exceeds 1050 ng/dL at the lowest daily dose of 30 mg (1 pump actuation), testosterone topical solution USP therapy should be discontinued.

The application site and dose of testosterone topical solution USP are not interchangeable with other topical testosterone products.

2.2 Administration Instructions

Testosterone topical solution USP is applied to the axilla, preferably at the same time each morning, to clean, dry, intact skin. Do not apply testosterone topical solution USP to other parts of the body including to the scrotum, penis, abdomen, shoulders or upper arms. After applying the solution, the application site should be allowed to dry completely prior to dressing. Avoid fire, flames or smoking until the solution has dried since alcohol based products, including testosterone topical solution USP, are flammable.

When deodorants or antiperspirants are used as part of a regular program for personal hygiene, they should not interfere with the efficacy of testosterone topical solution USP in treating hypogonadism. If patients use an antiperspirant or deodorant (stick or roll-on) then it should be applied at least 2 minutes prior to the application of testosterone topical solution USP to avoid contamination of the stick or roll-on product.

Patients should be advised to avoid swimming or washing the application site until two hours following application of testosterone topical solution USP [see CLINICAL PHARMACOLOGY (12.3)].

To reduce the likelihood of interpersonal transfer of testosterone, the application site should always be washed prior to any skin-to-skin contact regardless of the length of time since application. [see WARNINGS AND PRECAUTIONS (5.2)].

Testosterone topical solution USP is available as pump actuated metered-dose pump.

Pump Actuated Metered-Dose Pump

Testosterone topical solution USP is applied to the axilla using an applicator. When using testosterone topical solution USP for the first time, patients should be instructed to prime the pump by depressing the pump three times, discard any product dispensed directly into a basin, sink, or toilet and then wash the liquid away thoroughly. This priming should be done only prior to the first use of each pump. After priming, patients should completely depress the pump one time (1 pump actuation) to dispense 30 mg of testosterone. Ensure that the liquid is directed into the cup. The cup should be filled with no more than 30 mg (1 pump actuation) of testosterone. Dosing that requires greater than one pump actuation must be applied in increments of 30 mg as is shown in Table 1.

Keeping the applicator upright, patients should place it up into the axilla and wipe steadily down and up into the axilla. If the solution drips or runs, it can be wiped back up with the applicator cup. The solution should not be rubbed into the skin with fingers or hand. The process is then repeated with application of 30 mg of testosterone (1 pump actuation) to the other axilla to achieve a total of 60 mg of testosterone applied. For patients prescribed the 90 mg dose of testosterone, the procedure is the same, but three applications are required. To dose 120 mg of testosterone, four applications are required alternating left and right for each application as shown in Table 1. When repeat application to the same axilla is required, the axilla should be allowed to dry completely before more testosterone topical solution USP is applied.

After use, the applicator should be rinsed under room temperature, running water and then patted dry with a tissue. The applicator and cap are then replaced on the bottle for storage.

Table 1: Application Technique
Daily Prescribed Dose of Testosterone | Number of Pump Actuations | Application
30 mg (once daily) | 1 | Apply once to one axilla only (left OR right)
60 mg (once daily) | 2 | Apply once to the left axilla and then apply once to the right axilla.
90 mg (once daily) | 3 | Apply once to the left and once to the right axilla, wait for the product to dry, and then apply once again to the left OR right axilla.
120 mg (once daily) | 4 | Apply once to the left and once to the right axilla, wait for the product to dry, and then apply once again to the left AND once to the right axilla.

Hands should be washed thoroughly with soap and water after testosterone topical solution USP has been applied [see WARNINGS AND PRECAUTIONS (5.2)].

Strict adherence to the following precautions is advised in order to minimize the potential for secondary exposure to testosterone from testosterone topical solution USP treated skin:

- Children and women should avoid contact with the unclothed or unwashed application sites on the skin of men using testosterone topical solution USP.
- Patients should wash their hands immediately with soap and water after application of testosterone topical solution USP.
- Patients should cover the application site(s) with clothing (e.g., a T-shirt) after the solution has dried.
- Prior to any situation in which direct skin-to-skin contact is anticipated, patients should wash the application site thoroughly with soap and water to remove any testosterone residue.
- In the event that unwashed or unclothed skin to which testosterone topical solution USP has been applied comes in direct contact with the skin of another person, the general area of contact on the other person should be washed with soap and water as soon as possible.

While interpersonal testosterone transfer can occur with a T-shirt on, it has been shown that transfer can be substantially reduced by wearing a T-shirt and the majority of residual testosterone is removed from the skin surface by washing with soap and water.

3 DOSAGE FORMS AND STRENGTHS

Testosterone topical solution is a topical solution available as a:

- metered-dose pump that delivers 30 mg of testosterone per pump.

Each metered-dose pump is supplied with an applicator.

4 CONTRAINDICATIONS

- Testosterone topical solution is contraindicated in men with carcinoma of the breast or known or suspected carcinoma of the prostate [see WARNINGS AND PRECAUTION (5.1)] .
- Testosterone topical solution is contraindicated in women who are, or who may become pregnant, or who are breastfeeding. Testosterone topical solution may cause fetal harm when administered to a pregnant woman. Testosterone topical solution may cause serious adverse reactions in nursing infants. If a pregnant woman is exposed to testosterone topical solution, she should be apprised of the potential hazard to the fetus. [see USE IN SPECIFIC POPULATIONS (8.1,8.3)] .

5 WARNINGS AND PRECAUTIONS

5.1 Worsening of Benign Prostatic Hyperplasia and Potential Risk of Prostate Cancer

- Monitor patients with benign prostatic hyperplasia (BPH) for worsening of signs and symptoms of BPH.
- Patients treated with Androgens may be at increased risk for prostate cancer. Evaluate patients for prostate cancer prior to initiating treatment. It would be appropriate to reevaluate patients 3 to 6 months after initiation of treatment, and then in accordance with prostate cancer screening practices. [see CONTRAINDICATIONS (4)] .

5.2 Potential for Secondary Exposure to Testosterone

Cases of secondary exposure to testosterone in children and women have been reported with topical testosterone products applied to the abdomen or upper arms, including cases of secondary exposure resulting in virilization of children. Signs and symptoms have included enlargement of the penis or clitoris, development of pubic hair, increased erections and libido, aggressive behavior, and advanced bone age. In most cases, these signs and symptoms regressed with removal of the exposure to testosterone. In a few cases, however, enlarged genitalia did not fully return to age-appropriate normal size, and bone age remained modestly greater than chronological age. The risk of transfer was increased in some of these cases by not adhering to precautions for the appropriate use of the topical testosterone product. Children and women should avoid contact with unwashed or unclothed application sites in men using testosterone topical solution [see DOSAGE AND ADMINISTRATION (2.2), USE IN SPECIFIC POPULATIONS (8.1) and CLINICAL PHARMACOLOGY (12.3)].

Inappropriate changes in genital size or development of pubic hair or libido in children, or changes in body hair distribution, significant increase in acne, or other signs of virilization in adult women should be brought to the attention of a physician and the possibility of secondary exposure to testosterone should also be brought to the attention of a physician. Testosterone therapy should be promptly discontinued at least until the cause of virilization has been identified. [see DOSAGE AND ADMINISTRATION (2.2)].

5.3 Polycythemia

Increases in hematocrit, reflective of increases in red blood cell mass, may require lowering or discontinuation of testosterone. Check hematocrit prior to initiating testosterone treatment. It would be appropriate to re-evaluate the hematocrit 3 to 6 months after starting testosterone treatment, and then annually. If hematocrit becomes elevated, stop therapy until hematocrit decreases to an acceptable level. An increase in red blood cell mass may increase the risk of thromboembolic events.

5.4 Venous Thromboembolism

There have been postmarketing reports of venous thromboembolic events, including deep vein thrombosis (DVT) and pulmonary embolism (PE), in patients using testosterone products, such as testosterone topical solution. Evaluate patients who report symptoms of pain, edema, warmth and erythema in the lower extremity for DVT and those who present with acute shortness of breath for PE. If a venous thromboembolic event is suspected, discontinue treatment with testosterone topical solution and initiate appropriate workup and management [see ADVERSE REACTIONS (6.2)].

5.5 Cardiovascular Risk

Long term clinical safety trials have not been conducted to assess the cardiovascular outcomes of testosterone replacement therapy in men. To date, epidemiologic studies and randomized controlled trials have been inconclusive for determining the risk of major adverse cardiovascular events (MACE), such as non-fatal myocardial infarction, non-fatal stroke, and cardiovascular death, with the use of testosterone compared to non-use. Some studies, but not all, have reported an increased risk of MACE in association with use of testosterone replacement therapy in men. Patients should be informed of this possible risk when deciding whether to use or to continue to use testosterone topical solution.

5.6 Blood Pressure Increases

Testosterone products can increase blood pressure. Blood pressure increases can increase cardiovascular (CV) risk over time. Monitor blood pressure periodically in men using testosterone products, especially men with hypertension. Testosterone products are not recommended for use in patients with uncontrolled hypertension.

5.7 Abuse of Testosterone and Monitoring of Serum Testosterone Concentrations

Testosterone has been subject to abuse, typically at doses higher than recommended for the approved indication and in combination with other anabolic androgenic steroids. Anabolic androgenic steroid abuse can lead to serious cardiovascular and psychiatric adverse reactions [see DRUG ABUSE AND DEPENDENCE (9)].

If testosterone abuse is suspected, check serum testosterone concentrations to ensure they are within therapeutic range. However, testosterone levels may be in the normal or subnormal range in men abusing synthetic testosterone derivatives. Counsel patients concerning the serious adverse reactions associated with abuse of testosterone and anabolic androgenic steroids. Conversely, consider the possibility of testosterone and anabolic androgenic steroid abuse in suspected patients who present with serious cardiovascular or psychiatric adverse events.

5.8 Use in Women

Due to lack of controlled studies in women and potential virilizing effects, testosterone topical solution is not indicated for use in women [see CONTRAINDICATIONS (4) and USE IN SPECIFIC POPULATIONS (8.1, 8.3)].

5.9 Potential for Adverse Effects on Spermatogenesis

At large doses of exogenous androgens, including testosterone topical solution, spermatogenesis may be suppressed through feedback inhibition of pituitary follicle-stimulating hormone (FSH) which could possibly lead to adverse effects on semen parameters including sperm count.

5.10 Hepatic Adverse Effects

Prolonged use of high doses of orally active 17-alpha-alkyl androgens (methyltestosterone) has been associated with serious hepatic adverse effects (peliosis hepatitis, hepatic neoplasms, cholestatic hepatitis, and jaundice). Peliosis hepatitis can be a life-threatening or fatal complication. Long-term therapy with intramuscular testosterone enanthate has produced multiple hepatic adenomas. Testosterone topical solution is not known to cause these adverse effects.

5.11 Edema

Androgens, including testosterone topical solution, may promote retention of sodium and water. Edema, with or without congestive heart failure, may be a serious complication in patients with pre-existing cardiac, renal, or hepatic disease [see ADVERSE REACTIONS (6)].

5.12 Gynecomastia

Gynecomastia may develop and may persist in patients being treated with androgens, including testosterone topical solution, for hypogonadism.

5.13 Sleep Apnea

The treatment of hypogonadal men with testosterone may potentiate sleep apnea in some patients, especially those with risk factors such as obesity and chronic lung disease.

5.14 Lipids

Changes in serum lipid profile may require dose adjustment or discontinuation of testosterone therapy.

5.15 Hypercalcemia

Androgens, including testosterone topical solution, should be used with caution in cancer patients at risk of hypercalcemia (and associated hypercalciuria). Regular monitoring of serum calcium concentrations is recommended in these patients.

5.16 Decreased Thyroxine-binding Globulin

Androgens, including testosterone topical solution, may decrease concentrations of thyroxin-binding globulins, resulting in decreased total T4 serum concentration and increased resin uptake of T3 and T4. Free thyroid hormone concentration remain unchanged, however there is no clinical evidence of thyroid dysfunction.

5.17 Flammability

Alcohol based products, including testosterone topical solution, are flammable; therefore, patients should be advised to avoid smoking, fire or flame until the testosterone topical solution dose applied has dried.

6 ADVERSE REACTIONS

6.1 Clinical Trial Experience

Because clinical trials are conducted under widely varying conditions, adverse reaction rates observed in the clinical trials of a drug cannot be directly compared to rates in the clinical trials of another drug and may not reflect the rates observed in practice.

Clinical Trials in Hypogonadal Men

Table 2 shows the treatment emergent adverse reactions that were reported by either >4% of 155 patients in a 120 day, Phase 3 study or by >4% of 71 patients who continued to use testosterone topical solution for up to 180 days. These data reflect the experience primarily with a testosterone dose of 60 mg, which was taken by all patients at the start of the study, and was the maintenance dose for 97 patients. However, the doses used varied from 30 mg to 120 mg.

Event | 120 Days (155 Patients) | 180 Days (71 Patients)
Application Site Irritation | 11 (7%) | 6 (8%)
Application Site Erythema | 8 (5%) | 5 (7%)
Headache | 8 (5%) | 4 (6%)
Hematocrit Increased | 6 (4%) | 5 (7%)
Diarrhea | 4 (3%) | 3 (4%)
Vomiting | 4 (3%) | 3 (4%)
PSA Increased | 2 (1%) | 3 (4%)

Other less common adverse reactions reported by at least 2 patients in the 120 day trial included: application site edema, application site warmth, increased hemoglobin, hypertension, erythema (general), increased blood glucose, acne, nasopharyngitis, anger and anxiety. Other less common adverse reactions reported in fewer than 1% of patients in the 120 day trial included: asthenia, affect lability, folliculitis, increased lacrimation, breast tenderness, increased blood pressure, increased blood testosterone, neoplasm prostate and elevated red blood cell count.

During the 120 day trial one patient discontinued treatment because of affect lability/anger which was considered possibly related to testosterone topical solution administration.

During the 120 day clinical trial there was an increase in mean PSA values of 0.13 ± 0.68 ng/mL from baseline. At the end of the 180 day extension clinical trial, there was an overall increase in mean PSA values of 0.1 ± 0.54 ng/mL.

Following the 120 day study, seventy-one (71) patients entered a two-month extension study with testosterone topical solution. Two patients (3%) had adverse reactions that led to discontinuation of treatment during the period from Day 120 to Day 180. These reactions were: one patient with application site irritation (considered possibly related to testosterone topical solution application) and one patient with dry skin and erythema, but not at the application site (considered not related to testosterone topical solution administration) and application site erythema (considered possibly related to testosterone topical solution administration).

No serious adverse reactions to testosterone topical solution were reported during either the 120 day trial, or the extension to 180 days.

6.2 Postmarketing Experience

The following adverse reactions have been identified during postapproval use of testosterone topical solution. Because these reactions are reported voluntarily from a population of uncertain size, it is not always possible to reliably estimate their frequency or establish a causal relationship to drug exposure.

Cardiovascular Disorders

myocardial infarction, stroke [see WARNINGS AND PRECAUTIONS (5.5)].

Vascular Disorders

Venous thromboembolism [see WARNINGS AND PRECAUTIONS (5.4)].

7 DRUG INTERACTIONS

7.1 Insulin

Changes in insulin sensitivity or glycemic control may occur in patients treated with androgens. In diabetic patients, the metabolic effects of androgens may decrease blood glucose and, therefore, insulin requirement.

7.2 Oral anticoagulants

Changes in anticoagulant activity may be seen with androgens. More frequent monitoring of INR and prothrombin time is recommended in patients taking anticoagulants, especially at the initiation and termination of androgen therapy.

7.3 Corticosteroids

The concurrent use of testosterone with ACTH or corticosteroids may result in increased fluid retention and should be monitored cautiously, particularly in patients with cardiac, renal or hepatic disease.

8 USE IN SPECIFIC POPULATIONS

8.1 Pregnancy

Pregnancy Category X [see CONTRAINDICATIONS (4)]

Testosterone topical solution is contraindicated during pregnancy or in women who may become pregnant. Testosterone is teratogenic and may cause fetal harm. Exposure of a female fetus to androgens may result in varying degrees of virilization. If this drug is used during pregnancy, or if the patient becomes pregnant while taking this drug, the patient should be apprised of the potential hazard to a fetus.

8.3 Nursing Mothers

Although it is not known how much testosterone transfers into human milk, testosterone topical solution is contraindicated in nursing women because of the potential for serious adverse reactions in nursing infants. Testosterone and other androgens may adversely affect lactation. [see CONTRAINDICATIONS (4)].

8.4 Pediatric Use

Safety and efficacy of testosterone topical solution has not been established in males <18 years of age. Improper use may result in acceleration of bone age and premature closure of epiphyses.

8.5 Geriatric Use

There have not been sufficient numbers of geriatric patients involved in controlled clinical studies utilizing testosterone topical solution to determine whether efficacy in those over 65 years of age differs from younger patients. Of the 155 patients enrolled in the pivotal clinical study utilizing testosterone topical solution, 21 were over 65 years of age. Additionally, there were insufficient long-term safety data in these patients utilizing testosterone topical solution to assess a potential incremental risk of cardiovascular disease and prostate cancer.

8.6 Renal Impairment

No formal studies were conducted involving patients with renal impairment.

8.7 Hepatic Impairment

No formal studies were conducted involving patients with hepatic impairment.

8.8 Use in Men with Body Mass Index (BMI) >35 kg/m^2

Safety and efficacy of testosterone topical solution in males with BMI >35 kg/m^2has not been established.

9 DRUG ABUSE AND DEPENDENCE

9.1 Controlled Substance

Testosterone topical solution contains testosterone, a Schedule III controlled substance in the Controlled Substances Act.

9.2 Abuse

Drug abuse is intentional non-therapeutic use of a drug, even once, for its rewarding psychological and physiological effects. Abuse and misuse of testosterone are seen in male and female adults and adolescents. Testosterone, often in combination with other anabolic androgenic steroids (AAS), and not obtained by prescription through a pharmacy, may be abused by athletes and bodybuilders. There have been reports of misuse by men taking higher doses of legally obtained testosterone than prescribed and continuing testosterone despite adverse events or against medical advice.

Abuse-Related Adverse Reactions

Serious adverse reactions have been reported in individuals who abuse anabolic androgenic steroids and include cardiac arrest, myocardial infarction, hypertrophic cardiomyopathy, congestive heart failure, cerebrovascular accident, hepatotoxicity, and serious psychiatric manifestations, including major depression, mania, paranoia, psychosis, delusions, hallucinations, hostility and aggression.

The following adverse reactions have also been reported in men: transient ischemic attacks, convulsions, hypomania, irritability, dyslipidemias, testicular atrophy, subfertility, and infertility.

The following additional adverse reactions have been reported in women: hirsutism, virilization, deepening of voice, clitoral enlargement, breast atrophy, male-pattern baldness, and menstrual irregularities.

The following adverse reactions have been reported in male and female adolescents: premature closure of bony epiphyses with termination of growth, and precocious puberty.

Because these reactions are reported voluntarily from a population of uncertain size and may include abuse of other agents, it is not always possible to reliably estimate their frequency or establish a causal relationship to drug exposure.

9.3 Dependence

Behaviors Associated with Addiction

Continued abuse of testosterone and other anabolic steroids, leading to addiction is characterized by the following behaviors:

- Taking greater dosages than prescribed
- Continued drug use despite medical and social problems due to drug use
- Spending significant time to obtain the drug when supplies of the drug are interrupted
- Giving a higher priority to drug use than other obligations
- Having difficulty in discontinuing the drug despite desires and attempts to do so
- Experiencing withdrawal symptoms upon abrupt discontinuation of use

Physical dependence is characterized by withdrawal symptoms after abrupt drug discontinuation or a significant dose reduction of a drug. Individuals taking supratherapeutic doses of testosterone may experience withdrawal symptoms lasting for weeks or months which include depressed mood, major depression, fatigue, craving, restlessness, irritability, anorexia, insomnia, decreased libido and hypogonadotropic hypogonadism.

Drug dependence in individuals using approved doses of testosterone for approved indications has not been documented.

10 OVERDOSAGE

No cases of overdose with testosterone topical solution have been reported in clinical trials. There is one report of acute overdosage by injection of testosterone enanthate: testosterone concentrations of up to 11,400 ng/dL were implicated in a cerebrovascular accident. Treatment of overdosage would consist of discontinuation of testosterone topical solution together with appropriate symptomatic and supportive care.

11 DESCRIPTION

Testosterone topical solution USP is a clear, colorless, homogeneous solution containing 30 mg of testosterone USP in 1.5 mL of testosterone topical solution USP for topical administration through the axilla. The active pharmacologic ingredient in testosterone topical solution USP is testosterone USP. Testosterone USP is a white to practically white powder or crystals chemically described as 17-beta hydroxyandrost-4-en-3-one. The structural formula is:

The inactive ingredients are ethanol, isopropyl alcohol, octisalate and povidone.

12 CLINICAL PHARMACOLOGY

12.1 Mechanism of Action

Endogenous androgens, including testosterone and dihydrotestosterone (DHT), are responsible for the normal growth and development of the male sex organs and for maintenance of secondary sex characteristics. These effects include the growth and maturation of prostate, seminal vesicles, penis and scrotum; the development of male hair distribution, such as facial, pubic, chest and axillary hair; laryngeal enlargement, vocal cord thickening, alterations in body musculature and fat distribution. Testosterone and DHT are necessary for the normal development of secondary sex characteristics.

Male hypogonadism, a clinical syndrome resulting from insufficient secretion of testosterone, has two main etiologies. Primary hypogonadism is caused by defects of the gonads, such as Klinefelter's Syndrome or Leydig cell aplasia, whereas secondary hypogonadism is the failure of the hypothalamus (or pituitary) to produce sufficient gonadotropins (FSH, LH).

12.2 Pharmacodynamics

No specific pharmacodynamic studies were conducted using testosterone topical solution.

12.3 Pharmacokinetics

Absorption

Testosterone topical solution delivers physiologic circulating testosterone that approximate normal concentration range (i.e., 300 to 1050 ng/dL) seen in healthy men following application to the axilla.

On the skin, the ethanol and isopropyl alcohol evaporate leaving testosterone and octisalate. The skin acts as a reservoir from which testosterone is released into the systemic circulation over time (see Figure 1). In general, steady-state serum concentrations are achieved by approximately 14 days of daily dosing.

Figure 1: Mean (±SD) Serum Testosterone Concentrations on Day 7 in Patients Following Testosterone Topical Solution Once-Daily Application of 30 mg, 60 mg, or 90 mg of Testosterone

When testosterone topical solution treatment is discontinued after achieving steady-state, serum testosterone concentrations returned to their pretreatment concentrations by 7 to 10 days after the last application.

Distribution

Circulating testosterone is primarily bound in the serum to sex hormone-binding globulin (SHBG) and albumin. Approximately 40% of testosterone in plasma is bound to SHBG, 2% remains unbound (free) and the rest is bound to albumin and other proteins.

Metabolism

Testosterone is metabolized to various 17-keto steroids through two different pathways. The major active metabolites of testosterone are estradiol and dihydrotestosterone (DHT).

DHT concentration increased in parallel with testosterone concentration during testosterone topical solution treatment. The mean steady-state DHT/T ratio remained within normal limits and ranged from 0.17 to 0.26 across all doses on Days 15, 60, and 120.

Excretion

There is considerable variation in the half-life of testosterone as reported in the literature, ranging from 10 to 100 minutes. About 90% of a dose of testosterone given intramuscularly is excreted in the urine as glucuronic and sulfuric acid conjugates of testosterone and its metabolites; about 6% of a dose is excreted in the feces, mostly in the unconjugated form. Inactivation of testosterone occurs primarily in the liver.

Potential for Testosterone Transfer:

The potential for testosterone transfer from males dosed with testosterone topical solution to healthy females was evaluated in a clinical study conducted with a 2% testosterone formulation. 10 males were treated with 60 mg of testosterone in each axilla (the maximum testosterone dose of 120 mg). At 2 hours after the application of testosterone topical solution to the males, the females rubbed their outer forearms for 15 minutes on the axilla of the males. The males had covered the application area with a T-shirt. Serum concentrations of testosterone were monitored in the female subjects for 72 hours after the transfer procedure. Study results show a 13% and 17% increase in testosterone exposure (AUC[0 to 24]) and maximum testosterone concentration (Cmax), respectively, compared to baseline in these females. In a prior clinical study conducted with a 1% testosterone formulation under similar study conditions, direct skin-to-skin transfer showed a 131% and 297% increase in testosterone exposure (AUC[0 to 72]) and maximum testosterone concentration (Cmax), respectively, compared to when men had covered the application area with a T-shirt.

In a clinical study conducted with a 2% testosterone formulation to evaluate the effect of washing on the residual amount of testosterone at the axilla, 10 healthy male subjects received 60 mg of testosterone to each axilla (the maximum testosterone dose of 120 mg). Following 5 minutes of drying time, the left axilla was wiped with alcohol towelettes which were assayed for testosterone content. Subjects were required to shower with soap and water 30 minutes after application. The right axilla was then wiped with alcohol towelettes which were assayed for testosterone content. A mean (SD) of 3.1 (2.8) mg of residual testosterone (i.e., 92.6% reduction compared to when axilla was not washed) was recovered after washing this area with soap and water. [see DOSAGE AND ADMINISTRATION (2.2) and WARNINGS AND PRECAUTIONS (5.2)].

Use of Deodorants and Anti-perspirants:

In a parallel designed clinical study evaluating the effect of deodorants and antiperspirants in healthy premenopausal females dosed with testosterone topical solution, each subject applied either a combined deodorant/antiperspirant spray (6 subjects) or stick (6 subjects) or a deodorant spray (6 subjects) to a single axilla 2 minutes before the application of 30 mg of testosterone to the same axilla. A control group of 6 subjects only applied 30 mg of testosterone to a single axilla. Blood samples were collected for 72 hours from all subjects following testosterone topical solution administration. Although a decrease of up to 33% of testosterone exposure (AUC[0 to 72]) was observed when antiperspirants or deodorants are used 2 minutes prior to testosterone topical solution application, underarm deodorant or antiperspirant spray or stick products may be used 2 minutes prior to testosterone topical solution application as part of normal, consistent, and daily routine. [see DOSAGE AND ADMINISTRATION (2.2), and PATIENT COUNSELING INFORMATION (17.4)].

Effect of Showering/Washing:

In a parallel designed clinical study to evaluate the effect of washing on the testosterone systemic exposure, two groups of 6 healthy premenopausal female subjects were each dosed with 30 mg of testosterone to a single axilla. The application sites of each group were washed with soap and water 2 hours or 6 hours after the application of testosterone topical solution. A control group of 6 female subjects applied 30 mg of testosterone to a single axilla and did not wash the application site. Blood samples were collected for 72 hours from all subjects following dosing with testosterone topical solution. A decrease of up to 35% of testosterone exposure (AUC[0 to 72]) was observed when applications sites were washed 2 hours and 6 hours after testosterone topical solution application. Patients should be advised to avoid swimming or washing the application site until 2 hours following application of testosterone topical solution. [see DOSAGE AND ADMINISTRATION (2.2) and PATIENT COUNSELING INFORMATION (17.4)].

13 NONCLINICAL TOXICOLOGY

13.1 Carcinogenesis, Mutagenesis, Impairment of Fertility

Testosterone has been tested by subcutaneous injection and implantation in mice and rats. In mice, the implant induced cervical-uterine tumors, which metastasized in some cases. There is suggestive evidence that injection of testosterone into some strains of female mice increases their susceptibility to hepatoma. Testosterone is also known to increase the number of tumors and decrease the degree of differentiation of chemically induced carcinomas of the liver in rats. Testosterone was negative in the in vitro Ames and in the in vivo mouse micronucleus assays. The administration of exogenous testosterone has been reported to suppress spermatogenesis in the rat, dog and non-human primates, which was reversible on cessation of the treatment.

14 CLINICAL STUDIES

14.1 Clinical Studies in Hypogonadal Men

Testosterone topical solution was evaluated in a multicenter, open label, 120-day trial that enrolled 155 hypogonadal men at 26 clinical research centers. The median age of subjects was 53 years with a range of 19 to 78 years. Of the 144 subjects whose race was recorded, 122 (84.7%) were Caucasian, 13 (9.0%) were Hispanic, 6 (4.2%) were African Americans, 1 (0.7%) was Asian and 2 (1.4%) had race recorded as "Other".

Patients were instructed to apply testosterone topical solution to unclothed, clean, dry, and unbroken skin. The solution was applied to the axillary area. Patients were not instructed to alter their normal grooming routine, e.g., shave under the arm.

During the initial testosterone topical solution treatment period (Days 1 to 15) 143 patients were treated with 60 mg of testosterone daily. On Day 45 of the trial, patients were maintained at the same dose, or were titrated up or down, based on their 24 hour average serum testosterone concentration measured on Day 15. On Day 90 of the trial, patients were maintained at the same dose, or were titrated up or down, based on their 24 hour average serum testosterone concentration measured on Day 60.

On day 120, 75% of responding patients finished the study on the starting dose of 60 mg of testosterone, while 2% had been titrated to 30 mg, 17% had been titrated to 90 mg and 6% had been titrated to the 120 mg dose.

On day 60, 84.8% of subjects had total testosterone concentrations in the normal range. Of those who had sufficient data for analysis on day 120, 84.1%, had their average serum testosterone concentration in the normal range of 300 to 1050 ng/dL.

Table 3 summarizes the proportion of subjects having average testosterone concentrations within the normal range on Days 60 and 120.

Table 3: Proportion of subjects who had an average Serum Total Testosterone in the range 300 to 1050 ng/dL and completed 120 days of treatment (N=138 [Three patients who withdrew from the study due to adverse reactions are included as treatment failures.])
Evaluation Time | Statistics | Value
Baseline Testosterone | Mean (SD) | 194.6 ng/dL (92.9 ng/dL)
Day 15 | Normal [Normal represents the percentage of patients with average testosterone concentration in the range of 300 to 1050 ng/dL.] | 76.1% [On Day 15, 72.2% of the 90 subjects in the US study population had an average serum testosterone in the range of 300 ng/dL to 1050 ng/dL.]
 | 95% CI | (69.0%, 83.2%)
Day 60 | Normal | 84.8%
 | 95% CI | (78.8%, 90.8%)
Day 120 | Normal | 84.1%
 | 95% CI | (77.9%, 90.2%)

Of the 135 patients who completed the 120 day treatment, 123 patients did so with no deviation from the protocol. By day 120, average serum testosterone concentration was within normal range for 67% of those who titrated down on the 30 mg dose, 89% of those on the 60 mg dose, 86% of those who titrated up to 90 mg and 70% of those who titrated up to the 120 mg dose. Table 4 below summarizes the testosterone concentration data in the patients who completed 120 days.

Table 4: Baseline-unadjusted Arithmetic Mean (±SD) Steady-State Serum Testosterone Concentrations on Days 15, 60 and 120 in Patients Who Completed 120 Days of Treatment
 | Dose of Testosterone Topical Solution
 | 30 mg | 60 mg | 90 mg | 120 mg | Overall
Day 15 | [N=0] | [N=135] | [N=0] | [N=0] | [N=135]
Cavg (ng/dL) | -- | 456 (±226) | --- | -- | 456 (±226)
Cmax (ng/dL) | -- | 744 (±502) | -- | -- | 744 (±502)
Day 60 | [N=1] | [N=105] | [N=29] | [N=0] | [N=135]
Cavg (ng/dL) | 343 (--) | 523 (±207) | 368 (±138) | -- | 488 (±204)
Cmax (ng/dL) | 491 (--) | 898 (±664) | 646 (±382) | -- | 840 (±620)
Day 120 | [N=3] | [N=97] | [N=25] | [N=10] | [N=135]
Cavg (ng/dL) | 493 (±239) | 506 (±175) | 415 (±165) | 390 (±160) | 480 (±177)
Cmax (ng/dL) | 779 (±416) | 839 (±436) | 664 (±336) | 658 (±353) | 792 (±417)

Figure 2 summarizes the pharmacokinetic profiles of total testosterone in patients completing 120 days of testosterone topical solution treatment administered as 60 mg of testosterone for the initial 15 days followed by possible titration according to follow-up testosterone measurements.

Figure 2: Mean (± SD) Steady-State Serum Testosterone Concentrations on Day 120 (30, 60, 90 or 120 mg testosterone) in Patients Who Completed 120 Days (N=135) of Testosterone Topical Solution Once-Daily Treatment

16 HOW SUPPLIED/STORAGE AND HANDLING

16.1 How Supplied

Testosterone topical solution USP is available as a metered-dose pump containing 110 mL of solution. The pump is capable of dispensing 90 mL of solution in 60 metered pump actuations. One actuation delivers 30 mg of testosterone in 1.5 mL of solution. Each metered-dose pump is supplied with an applicator. The bottle and the applicator cup are not made with natural rubber latex.

NDC | Pump Type
68180-943-11 | Pump Actuated

16.2 Storage and Handling

Keep testosterone topical solution out of reach of children.

Store upright at 25°C (77°F); excursions permitted to 15° to 30°C (59° to 86°F) [see USP Controlled Room Temperature].

Used testosterone topical solution bottles and applicators should be discarded in household trash in a manner that prevents accidental exposure of children or pets.

17 PATIENT COUNSELING INFORMATION

See FDA-Approved Medication Guide.

Patients should be informed of the following information:

17.1 Use in Men with Known or Suspected Prostate or Breast Cancer

Men with known or suspected prostate or breast cancer should not use testosterone topical solution [see CONTRAINDICATIONS (4) and WARNINGS AND PRECAUTION (5.1)].

17.2 Potential for Secondary Exposure to Testosterone and Steps to Prevent Secondary Exposure

Cases of secondary exposure to testosterone in children and women have been reported with topical testosterone products applied to the abdomen, shoulders or upper arms, including cases of secondary exposure resulting in virilization of children, with signs and symptoms including enlargement of the penis or clitoris, premature development of pubic hair, increased erections, aggressive behavior and advanced bone age. Inappropriate changes in genital size or premature development of pubic hair or libido in children, or changes in hair distribution, increase in acne, or other signs of testosterone effects in adult women should be brought to the attention of a physician and the possibility of secondary exposure to testosterone topical solution also should be brought to the attention of a physician. Testosterone topical solution should be promptly discontinued at least until the cause of virilization is identified.

Strict adherence to the following precautions is advised in order to minimize the potential for secondary exposure to testosterone from testosterone topical solution treated skin:

- Testosterone topical solution should only be applied to the axilla, not to any other part of the body.
- Children and women should avoid contact with the unwashed skin of the axilla or unclothed application sites of men where testosterone topical solution has been applied.
- Patients should wash their hands immediately with soap and water after application of testosterone topical solution.
- Patients should cover the axilla application site(s) with clothing (e.g., a shirt) after waiting 3 minutes for the solution to dry.
- Prior to any situation in which direct skin-to-skin contact of the axilla is anticipated, patients should wash the axilla to which testosterone topical solution has been applied thoroughly with soap and water to remove any testosterone residue.
- In the event that unwashed or unclothed skin to which testosterone topical solution has been applied comes in direct contact with the skin of another person, the general area of contact on the other person should be washed with soap and water as soon as possible [see DOSAGE AND ADMINISTRATION (2.2), WARNINGS AND PRECAUTIONS (5.2) and CLINICAL PHARMACOLOGY (12.3)] .

17.3 Potential Adverse Reactions with Androgens

Patients should be informed that treatment with Androgens may lead to adverse reactions which include:

- Changes in urinary habits such as increased urination at night, trouble starting your urine stream, passing urine many times during the day, having an urge that you have to go to the bathroom right away, having urine accident, being unable to pass urine and having a weak urine flow.
- Breathing disturbances, including those associated with sleep, or excessive daytime sleepiness.
- Too frequent or persistent erections of the penis.
- Nausea, vomiting, changes in skin color, or ankle swelling.

17.4 Patients should be advised of these Application Instructions

- Ensure that the patient understands how to administer the correct dose.
- The pump should be primed by depressing it 3 times prior to its first use. No priming is needed with subsequent uses of that pump.
- Testosterone topical solution should NOT be applied to the scrotum, penis, abdomen, shoulders or upper arms.
- With testosterone doses greater than 60 mg, which require two applications of testosterone topical solution to the same axilla, the product should be allowed to dry after the first application before the second is applied.
- Testosterone topical solution should be applied once daily at approximately the same time each day. Testosterone topical solution should be applied to clean, dry skin.
- Patients may use an antiperspirant or deodorant spray before applying testosterone topical solution. If patients use a stick or roll-on antiperspirant or deodorant, then it should be applied at least 2 minutes prior to application of testosterone topical solution to avoid contamination of the stick or roll-on product.
- Avoid swimming or washing the application site until two hours following application of testosterone topical solution [see DOSAGE AND ADMINISTRATION (2) and CLINICAL PHARMACOLOGY (12.3)] .
- Avoid splashing in the eyes. In case of contact with eyes, flush thoroughly with water. If irritation persists, seek medical advice.
- Do not drink testosterone topical solution.

LUPIN and the are registered trademarks of Lupin Pharmaceuticals, Inc.

Manufactured for:

Lupin Pharmaceuticals, Inc.

Naples, FL 34108

United States

Manufactured by:

Lupin Limited

Pithampur (M.P.) – 454 775

India

March 2025 ID#:280120

MEDICATION GUIDE

Testosterone (tes TOS ter one) Topical Solution USP, for topical use CIII

What is the most important information I should know about testosterone topical solution?

1. Testosterone topical solution can transfer from your body to others including, children and women. Children and women should avoid contact with the unwashed or not covered (unclothed) areas where testosterone topical solution has been applied to your skin. Early signs and symptoms of puberty have occurred in young children who have come in direct contact with testosterone by touching areas where men have used testosterone topical solution.

Children

Signs and symptoms of early puberty in a child when they come in direct contact with testosterone topical solution may include:

Abnormal sexual changes:

- enlarged penis or clitoris.
- early growth of hair near the vagina or around the penis (pubic hair).
- erections or acting out sexual urges (sex drive).

Behavior problems:

- acting aggressively, behaving in an angry or violent way.

Women

Signs and symptoms in women when they come in direct contact with testosterone topical solution may include:

- changes in body hair.
- an abnormal increase in pimples (acne).

Stop using testosterone topical solution and call your healthcare provider right away if you see any signs and symptoms in a child or a woman that may have happened through accidental touching of the area where you have applied testosterone topical solution:

2. To lower the risk of transfer of testosterone topical solution from your body to others, follow these important instructions:

- Apply testosterone topical solution only to your armpits.
- Wash your hands right away with soap and water after applying testosterone topical solution.
- After the solution has dried, cover the application area with clothing. Keep the area covered until you have washed the application area well or have showered.
- If you expect to have skin-to-skin contact with another person, first wash the application area well with soap and water.
- If a child or woman touches the area where you have applied testosterone topical solution, that area on the child or woman should be washed well with soap and water right away.

What is testosterone topical solution?

- Testosterone topical solution is a prescription medicine that contains testosterone. Testosterone topical solution is used to treat adult males who have low or no testosterone due to certain medical conditions.
  - Your healthcare provider will test your blood before you start and while you are using testosterone topical solution.
  - It is not known if testosterone topical solution is safe or effective to treat men who have low testosterone due to aging.
  - It is not known if testosterone topical solution is safe and effective in children younger than 18 years old. Improper use of testosterone topical solution may affect bone growth in children.
- Testosterone topical solution is a controlled substance (CIII) because it contains testosterone that can be a target for people who abuse prescription medicines. Keep your testosterone topical solution in a safe place to protect it. Never give testosterone topical solution to anyone else, even if they have the same symptoms you have. Selling or giving away this medicine may harm others and it is against the law.
- Testosterone topical solution is not meant for use in women.

Do not use testosterone topical solution if you:

- have breast cancer.
- have or might have prostate cancer.
- are pregnant or may become pregnant or are breastfeeding. Testosterone topical solution may harm your unborn or breastfeeding baby.

Women who are pregnant or who may become pregnant should avoid contact with the area of the skin where testosterone topical solution has been applied.

Before using testosterone topical solution, tell your healthcare provider about all of your medical conditions, including if you:

- have breast cancer.
- have or might have prostate cancer.
- have urinary problems due to an enlarged prostate.
- have high blood pressure or are being treated for high blood pressure.
- have heart problems.
- have kidney or liver problems.
- have problems breathing while you sleep (sleep apnea).

Tell your healthcare provider about all of the medicines you take, including prescription and over-the-counter medicines, vitamins, and herbal supplements. Using testosterone topical solution with other medicines can affect each other.

Especially tell your healthcare provider if you take:

- insulin
- medicines that decrease blood clotting (blood thinners)
- corticosteroids

How should I use testosterone topical solution?

- See the detailed Instructions for Use for information about how to use testosterone topical solution at the end of this Medication Guide.
- Testosterone topical solution comes in a metered-dose pump or twist actuated dispenser. Make sure you have the right pump or dispenser that is prescribed for you.
- It is important that you apply testosterone topical solution exactly as your healthcare provider tells you to.
- Your healthcare provider may change your testosterone topical solution dose. Do not change your testosterone topical solution dose without talking to your healthcare provider.
- Apply testosterone topical solution at about the same time each morning. Testosterone topical solution should be applied after showering or bathing.

What are the possible side effects of testosterone topical solution?

Testosterone topical solution can cause serious side effects including:

See also "What is the most important information I should know about testosterone topical solution?"

- If you already have an enlarged prostate, your symptoms can get worse while using testosterone topical solution. This can include:
  - increased urination at night.
  - trouble starting your urine stream.
  - having to pass urine many times during the day.
  - having an urge to go to the bathroom right away.
  - having a urine accident.
  - being unable to pass urine or weak urine flow.

- Possible increased risk of prostate cancer. Your healthcare provider should check you for prostate cancer or any other prostate problems before you start and while you use testosterone topical solution.
- Blood clots in the legs or lungs. Signs and symptoms of a blood clot in your leg can include leg pain, swelling or redness. Signs and symptoms of a blood clot in your lungs can include difficulty breathing or chest pain.
- Possible increased risk of heart attack or stroke.
- In large doses testosterone topical solution may lower your sperm count.
- Swelling of your ankles, feet, or body, with or without heart failure.
- Enlarged or painful breasts.
- Have problems breathing while you sleep (sleep apnea).

Call your healthcare provider right away if you have any of the serious side effects listed above.

The most common side effects of testosterone topical solution include:

- skin redness or irritation where testosterone topical solution is applied
- increased red blood cell count
- headache
- diarrhea
- vomiting
- increase in blood level of Prostate Specific Antigen (a test used to screen for prostate cancer)

Other side effects include more erections than are normal for you or erections that last a long time.

Tell your healthcare provider if you have any side effect that bothers you or that does not go away.

These are not all the possible side effects of testosterone topical solution. For more information, ask your healthcare provider or pharmacist.

Call your doctor for medical advice about side effects. You may report side effects to FDA at 1-800-FDA-1088.

General information about the safe and effective use of testosterone topical solution.

Medicines are sometimes prescribed for purposes other than those listed in a Medication Guide. Do not use testosterone topical solution for a condition for which it was not prescribed. Do not give testosterone topical solution to other people, even if they have the same symptoms you have. It may harm them.

You can ask your pharmacist or healthcare provider for information about testosterone topical solution that is written for health professionals.

What are the ingredients in testosterone topical solution?

Active ingredient: testosterone USP.

Inactive ingredients: ethanol, isopropyl alcohol, octisalate, and povidone.

The bottle and the applicator cup are not made with natural rubber latex.

For more information, go to www.lupinpharmaceuticals.com or call 1-800-399-2561.

This Medication Guide has been approved by the U.S. Food and Drug Administration.

INSTRUCTIONS FOR USE

Testosterone (tes TOS ter one) Topical Solution USP, for topical use, CIII

Read this Instructions for Use for testosterone topical solution before you start using it and each time you get a refill. There may be new information. This leaflet does not take the place of talking to your healthcare provider about your medical condition or treatment.

Applying Testosterone Topical Solution:

- Testosterone topical solution is to be applied to the armpits only. Do not apply mtestosterone topical solution to any other parts of your body such as your stomach area (abdomen), penis, scrotum, shoulders or upper arms.
- Do not apply testosterone topical solution with your fingers or hands.
- Apply testosterone topical solution at about the same time each morning. Testosterone topical solution should be applied after showering or bathing.
- Avoid swimming or bathing for at least 2 hours after you apply testosterone topical solution.
- You can use an antiperspirant or deodorant before applying testosterone topical solution. If you use antiperspirant or deodorant, then it should be applied at least 2 minutes before you apply testosterone topical solution.
- Testosterone topical solution is flammable until dry. Let testosterone topical solution dry before smoking or going near an open flame.
- Avoid splashing in the eyes. In case of contact with eyes, flush thoroughly with water. If irritation persists, seek medical advice.

Testosterone Topical Solution Figure 1

- Before using a new bottle of testosterone topical solution for the first time, you will need to prime the pump. To prime the testosterone topical solution pump gently push down on the pump 3 times. Do not use any testosterone topical solution that came out while priming. Wash it down the sink to avoid accidental exposure to others. Your testosterone topical solution pump is now ready to use.
- Use testosterone topical solution exactly as your healthcare provider tells you to use it. Your healthcare provider will tell you the dose of testosterone topical solution that is right for you. Apply your dose correctly by following the application instructions in the table below.

Find Your Dose as Prescribed by Your Healthcare Provider | Each application equals 1 press (depression) of the pump.
30 mg | Apply 1 application one time to one armpit only (left or right).
60 mg | Apply 2 applications: one to the left armpit and then one to the right armpit.
90 mg | Apply 3 applications: one to the left and one to the right armpit, wait for the product to dry, and then apply again one to the left or right armpit.
120 mg | Apply 4 applications: one to the left and one to the right armpit, wait for the product to dry, and then apply again one to the left and one to the right armpit.

- Before applying testosterone topical solution, make sure that your armpit is clean, dry and that there is no broken skin.

Figure 2

- Remove the cap and the applicator cup from the pump. Then, position the nozzle over the applicator cup and gently press down on (depress) the pump (see Figure 2).

Figure 3

- To apply the testosterone topical solution, keep the applicator upright, place it up into the armpit application site and wipe steadily down and up (see Figure 3).
- If testosterone topical solution drips or runs, wipe it back up with the applicator cup. Do not rub in the solution with your fingers or hand after it has been applied.
- Let the application site dry completely for 3 minutes before putting on a shirt.
- After you have finished applying testosterone topical solution, rinse the applicator cup with room temperature running water, and then pat it dry with a tissue. Carefully replace the applicator cup and cap back onto the bottle and make sure you store the bottle safely.
- Clean up any spilled solution from surfaces such as the sink or floor to make sure others do not come into contact with it.
- Wash your hands with soap and water right away.

How should I store testosterone topical solution?

- Store testosterone topical solution upright at room temperature between 68°F to 77°F (20°C to 25°C).
- When it is time to throw away the bottle, safely throw away all parts of the testosterone topical solution dispenser including the bottle applicator cup and cap into the household trash.
- Be careful to prevent accidental exposure of children or pets.
- Keep testosterone topical solution away from fire.

Keep testosterone topical solution and all medicines out of the reach of children.

This Instructions for Use has been approved by the U.S. Food and Drug Administration.

LUPIN and the are registered trademarks of Lupin Pharmaceuticals, Inc.

Manufactured for:

Lupin Pharmaceuticals, Inc.

Naples, FL 34108

United States

Manufactured by:

Lupin Limited

Pithampur (M.P.) – 454 775

India

March 2024 ID#: 280140

PACKAGE LABEL.PRINCIPAL DISPLAY PANEL

Testosterone Topical Solution

30 mg of testosterone per pump actuation CIII

Each actuation delivers 1.5 mL of solution

Multi-dose pump capable of dispensing 60 metered pump actuations.

For topical use only with enclosed applicator

Dispense the enclosed Medication Guide to each patient

Rx Only

NDC 68180-943-11

Carton Label

Testosterone Topical Solution

30 mg of testosterone per pump actuation CIII

Each actuation delivers 1.5 mL of solution

Multi-dose pump capable of dispensing 60 metered pump actuations.

For topical use only with enclosed applicator

Dispense the enclosed Medication Guide to each patient

Rx Only

NDC 68180-943-11

Container Label